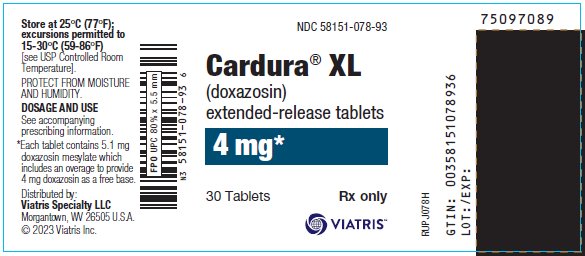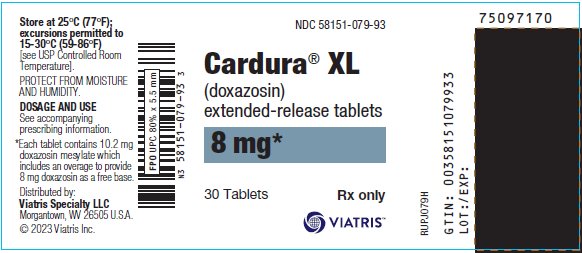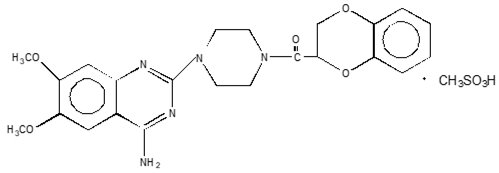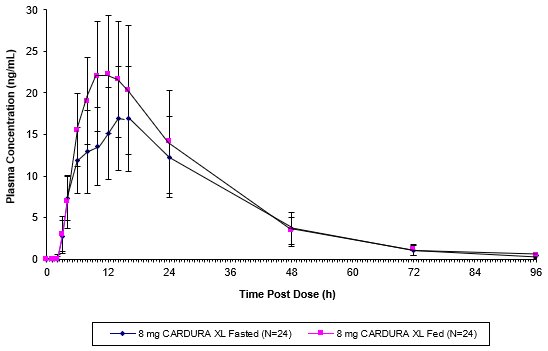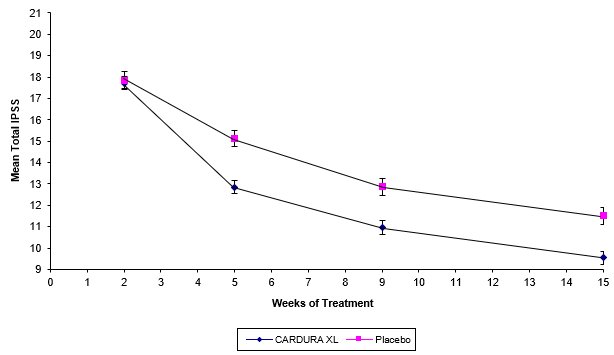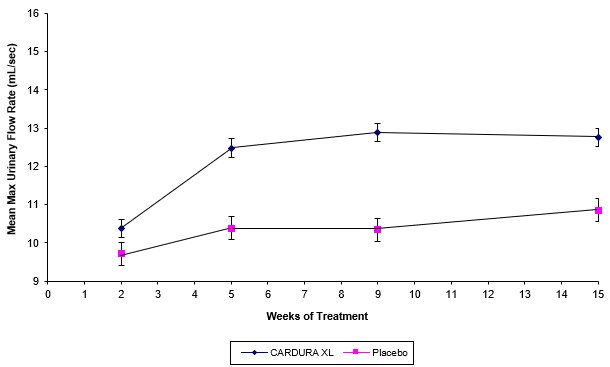 DRUG LABEL: Cardura
NDC: 58151-078 | Form: TABLET, FILM COATED, EXTENDED RELEASE
Manufacturer: Viatris Specialty LLC
Category: prescription | Type: HUMAN PRESCRIPTION DRUG LABEL
Date: 20230515

ACTIVE INGREDIENTS: DOXAZOSIN MESYLATE 4 mg/1 1
INACTIVE INGREDIENTS: FERROSOFERRIC OXIDE; CELLULOSE ACETATE; HYPROMELLOSE, UNSPECIFIED; POLYETHYLENE GLYCOL, UNSPECIFIED; MAGNESIUM STEARATE; SHELLAC; FERRIC OXIDE RED; SODIUM CHLORIDE; TITANIUM DIOXIDE

HIGHLIGHTS OF PRESCRIBING INFORMATION

These highlights do not include all the information needed to use CARDURA XL safely and effectively. See full prescribing information for CARDURA XL.
CARDURA® XL (doxazosin) extended-release tablets, for oral use
Initial U.S. Approval: 1990

1 INDICATIONS AND USAGE

CARDURA XL is an alpha1 adrenergic antagonist indicated for the treatment of the signs and symptoms of benign prostatic hyperplasia. (1)

CARDURA XL is not indicated for the treatment of hypertension. (1)

2 DOSAGE AND ADMINISTRATION

Recommended starting dose (initial therapy or switching from immediate-release): 4 mg once daily with breakfast (2.1, 2.2)

Dose range: 4 to 8 mg once daily (2.1)

3 DOSAGE FORMS AND STRENGTHS

4 mg and 8 mg tablets (3)

4 CONTRAINDICATIONS

Patients with known sensitivity to doxazosin, other quinazolines, or any of the inert ingredients (4)

5 WARNINGS AND PRECAUTIONS

Postural hypotension with or without syncope may occur in the first few hours after administration. (5.1)

Intraoperative Floppy Iris Syndrome has been observed during cataract surgery in some patients. Advise patients considering cataract surgery to tell their ophthalmologist that they have taken CARDURA XL tablets. (5.2)

Caution should be used when administering to patients with preexisting severe gastrointestinal narrowing or coronary insufficiency. (5.3, 5.7)

Advise patients to be screened for the presence of prostate cancer prior to treatment and at regular intervals afterwards. (5.4)

6 ADVERSE REACTIONS

The most commonly reported adverse reactions from clinical trials are asthenia, headache, hypotension, and dizziness. (6.1)

To report SUSPECTED ADVERSE REACTIONS, contact Viatris at 1-877-446-3679 (1-877-4-INFO-RX) or FDA at 1-800-FDA-1088 or www.fda.gov/medwatch.

7 DRUG INTERACTIONS

Caution should be exercised when concomitantly administering CARDURA XL with a strong cytochrome P450 (CYP) 3A4 inhibitor. (7.1)

Concomitant administration of CARDURA XL with a phosphodiesterase-5 (PDE-5) inhibitor can result in additive blood pressure lowering effects and symptomatic hypotension. (7.3)

8 USE IN SPECIFIC POPULATIONS

Geriatric: Hypotension with CARDURA XL is more prevalent in patients 70 years or older. (8.5)

Hepatic Impairment: CARDURA XL is not recommended for patients with severe hepatic impairment and should be administered with caution to patients with mild or moderate hepatic impairment. (8.6, 12.3)

FULL PRESCRIBING INFORMATION

1 INDICATIONS AND USAGE

CARDURA® XL is indicated for the treatment of the signs and symptoms of benign prostatic hyperplasia (BPH).

CARDURA XL is not indicated for the treatment of hypertension.

2 DOSAGE AND ADMINISTRATION

2.1 General Dosing Information

The initial dose of CARDURA XL, 4 mg given once daily, should be administered with breakfast. Depending on the patient’s symptomatic response and tolerability, the dose may be increased to 8 mg, the maximum recommended dose. The recommended titration interval is 3-4 weeks. If CARDURA XL administration is discontinued for several days, therapy should be restarted using the 4 mg once daily dose. Tablets should be swallowed whole, and must not be chewed, divided, cut, or crushed.

2.2 Patients Switching from CARDURA to CARDURA XL

If switching from CARDURA immediate-release (IR) to CARDURA XL, therapy should be initiated with the lowest dose (4 mg once daily). Prior to starting therapy with CARDURA XL, the final evening dose of CARDURA should not be taken.

2.3 Concomitant Administration with PDE-5 Inhibitors

Concomitant administration of CARDURA XL with a PDE-5 inhibitor can result in additive blood pressure lowering effects and symptomatic hypotension; therefore, PDE-5 inhibitor therapy should be initiated at the lowest dose in patients taking CARDURA XL.

3 DOSAGE FORMS AND STRENGTHS

White, round, film-coated tablets containing doxazosin mesylate equivalent to 4 mg and 8 mg doxazosin (free base).

4 CONTRAINDICATIONS

CARDURA XL is contraindicated in patients with a known hypersensitivity to doxazosin, other quinazolines (e.g., prazosin, terazosin), or any of the inert ingredients. Allergic reactions to doxazosin and other quinazolines have included skin rash, urticaria, pruritus, angioedema, and respiratory symptoms [see Adverse Reactions (6.2)].

5 WARNINGS AND PRECAUTIONS

5.1 Postural Hypotension

Postural hypotension with or without symptoms (e.g., dizziness) may develop within a few hours following administration of CARDURA XL. However, infrequently, symptomatic postural hypotension has also been reported later than a few hours after dosing. As with other alpha-blockers, there is a potential for syncope, especially after the initial dose or after an increase in dosage strength. Patients should be warned of the possible occurrence of such events and should avoid situations where injury could result should syncope occur. Care should be taken when CARDURA XL is administered to patients with symptomatic hypotension or patients who have had a hypotensive response to other medications.

5.2 Cataract Surgery

Intraoperative Floppy Iris Syndrome (IFIS) has been observed during cataract surgery in some patients on or previously treated with alpha1 blockers. This variant of small pupil syndrome is characterized by the combination of a flaccid iris that billows in response to intraoperative irrigation currents, progressive intraoperative miosis despite preoperative dilation with standard mydriatic drugs, and potential prolapse of the iris toward the phacoemulsification incisions. The patient’s surgeon should be prepared for possible modifications to their surgical technique, such as the utilization of iris hooks, iris dilator rings, or viscoelastic substances. There does not appear to be a benefit from stopping alpha1 blocker therapy prior to cataract surgery.

5.3 Gastrointestinal Disorders

As with any other non-deformable material, caution should be used when administering CARDURA XL to patients with preexisting severe gastrointestinal narrowing (pathologic or iatrogenic). There have been rare reports of obstructive symptoms in patients with known strictures in association with the ingestion of another drug in this non-deformable extended-release formulation. Markedly increased GI retention times, as may occur in patients with chronic constipation, can increase systemic exposure to doxazosin and thereby potentially increase adverse reactions.

5.4 Prostate Cancer

Carcinoma of the prostate causes many of the same symptoms associated with BPH and the two disorders frequently co-exist. Carcinoma of the prostate should therefore be ruled out prior to commencing therapy with CARDURA XL.

5.5 PDE-5 Inhibitors

Concomitant administration of CARDURA XL with a PDE-5 inhibitor can result in additive blood pressure lowering effects and symptomatic hypotension. Pharmacodynamic interactions between CARDURA XL and antihypertensive medications or other vasodilating agents have not been determined.

5.6 Patients with Hepatic Impairment

CARDURA XL is not recommended for patients with severe hepatic impairment and should be administered with caution to patients with mild or moderate hepatic impairment [see Use in Specific Populations (8.6), Clinical Pharmacology (12.3)].

5.7 Patients with Coronary Insufficiency

Patients with congestive heart failure, angina pectoris, or acute myocardial infarction within the last 6 months were excluded from the Phase 3 studies. If symptoms of angina pectoris should newly appear or worsen, CARDURA XL should be discontinued.

5.8 CYP 3A4 Inhibitors

Caution should be exercised when concomitantly administering CARDURA XL with a strong CYP 3A4 inhibitor, such as atazanavir, clarithromycin, indinavir, itraconazole, ketoconazole, nefazodone, nelfinavir, ritonavir, saquinavir, telithromycin, or voriconazole.

5.9 Priapism

Rarely (probably less frequently than once in every several thousand patients), alpha-1 antagonists, including doxazosin, have been associated with priapism (painful penile erection, sustained for hours and unrelieved by sexual intercourse or masturbation). Because this condition can lead to permanent impotence if not promptly treated, patients must be advised about the seriousness of the condition.

6 ADVERSE REACTIONS

6.1 Clinical Trials Experience

Because clinical trials are conducted under widely varying conditions, adverse reaction rates observed in the clinical trials of a drug cannot be directly compared to rates in the clinical trials of another drug and may not reflect the rates observed in clinical practice.

The incidence of adverse reactions was derived from two controlled efficacy and safety trials involving 1473 BPH patients. In Study 1, CARDURA XL (n = 317) was compared to doxazosin IR tablets (n = 322) and to placebo (n = 156). In Study 2, CARDURA XL (n = 350) was compared just to doxazosin IR tablets (n = 330). In both of these studies, CARDURA XL was initiated at a dose of 4 mg, which could be increased by the investigator to 8 mg after seven weeks if an adequate response was not seen [see Clinical Studies (14.1)]. Similarly, doxazosin IR was begun at a dose of 1 mg, which was increased in all patients to 2 mg after 1 week, followed by the option to increase to 4 mg after 4 weeks, and 8 mg after 7 weeks.

The most commonly reported adverse reactions leading to discontinuation in the CARDURA XL group were dizziness, dyspnea, asthenia, headache, hypotension, postural hypotension, and somnolence. The rates of discontinuation for adverse reactions were 6%, 7% and 3% in the CARDURA XL, doxazosin IR, and placebo groups, respectively.

Table 1 lists the incidence rates of adverse reactions derived from all reported adverse events in the two controlled studies (Studies 1 and 2) combined, at a rate greater than placebo and in 1% or more of patients treated with CARDURA XL.

TABLE 1
Adverse Reactions, Derived from All Adverse Events Exceeding Placebo Rate and Occurring in ≥ 1% of BPH Patients Treated with CARDURA XL
Body System | CARDURA XL; (N = 666) | Doxazosin IR; (N = 651) | Placebo; (N = 156)
BODY AS A WHOLE
Abdominal Pain | 1.8% | 2.3% | 0.6%
Asthenia | 3.9% | 6.9% | 1.3%
Headache | 6.0% | 5.1% | 4.5%
CARDIOVASCULAR
Hypotension | 1.7% | 1.8% | 0.0%
Postural Hypotension | 1.2% | 2.2% | 0.6%
DIGESTIVE
Dyspepsia | 1.4% | 1.2% | 0.0%
Nausea | 1.2% | 2.3% | 0.6%
MUSCULOSKELETAL
Myalgia | 1.4% | 0.5% | 0.0%
NERVOUS
Dizziness | 5.3% | 9.1% | 1.9%
Somnolence | 1.5% | 1.2% | 0.0%
Vertigo | 1.5% | 4.1% | 0.6%
RESPIRATORY
Dyspnea | 1.2% | 1.2% | 0.0%
Respiratory Tract Infection | 4.8% | 4.5% | 1.9%
UROGENITAL
Urinary Tract Infection | 1.4% | 0.8% | 0.6%

Additional adverse events reported with CARDURA XL, reported by less than 1% of patients, and those of clinical interest include:

Cardiovascular System: angina pectoris, syncope, tachycardia, chest pain, palpitations;

Digestive System: diarrhea;

Musculoskeletal System: arthralgia;

Nervous System: libido decreased;

Urogenital System: impotence, dysuria.

In general, the adverse events reported in the open-label safety extension, in approximately 295 BPH patients treated for up to 37 weeks, were similar in type and frequency to the events described above in the controlled trials.

6.2 Postmarketing Experience

The following adverse events have been identified during post-approval use of doxazosin. Because these reactions are reported voluntarily from a population of uncertain size, it is not always possible to reliably estimate their frequency or establish a causal relationship to drug exposure.

Autonomic Nervous System: priapism;

Cardiovascular System: cerebrovascular accidents, dizziness postural, myocardial infarction;

Central and Peripheral Nervous System: hypoesthesia, paresthesia;

Endocrine System: gynecomastia;

Gastrointestinal System: gastrointestinal obstruction, vomiting;

General Body System: fatigue, hot flushes, malaise;

Heart Rate/Rhythm: bradycardia, cardiac arrhythmias;

Hematopoietic: leukopenia, purpura, thrombocytopenia;

Liver/Biliary System: abnormal liver function tests, hepatitis, hepatitis cholestatic, jaundice;

Musculoskeletal System: muscle cramps, muscle weakness;

Psychiatric: agitation, anorexia, nervousness;

Respiratory System: bronchospasm aggravated;

Skin Disorders: alopecia, urticaria, skin rash, pruritus;

Special Senses: blurred vision, Intraoperative Floppy Iris Syndrome [see Warnings and Precautions (5.2)];

Urinary System: hematuria, micturition disorder, micturition frequency, nocturia, polyuria.

There have been rare reports of gastrointestinal irritation and gastrointestinal bleeding with use of another drug in this non-deformable sustained release formulation, although causal relationship to the drug is uncertain.

7 DRUG INTERACTIONS

7.1 CYP 3A4 Inhibitors

No in vivo drug interaction studies were conducted with CARDURA XL.

In vitro studies suggest that doxazosin is a substrate of CYP 3A4. Caution should be exercised when concomitantly administering CARDURA XL with a strong CYP 3A4 inhibitor, such as atazanavir, clarithromycin, indinavir, itraconazole, ketoconazole, nefazodone, nelfinavir, ritonavir, saquinavir, telithromycin, or voriconazole [see Clinical Pharmacology (12.3)].

7.2 Antihypertensive Medications

Pharmacodynamic interactions between CARDURA XL and antihypertensive medications or other vasodilating agents have not been determined.

7.3 PDE-5 Inhibitors

Concomitant administration of CARDURA XL with a PDE-5 inhibitor can result in additive blood pressure lowering effects and symptomatic hypotension [see Dosage and Administration (2.3)].

8 USE IN SPECIFIC POPULATIONS

8.1 Pregnancy

Risk Summary

CARDURA XL is not indicated for use in females and is not indicated for the treatment of hypertension. The limited available data with CARDURA XL in pregnant women are not sufficient to inform a drug-associated risk for major birth defects and miscarriage. No adverse developmental outcomes were observed in animal reproduction studies with oral administration of doxazosin to pregnant rats and rabbits at doses of up to 10 and 4 times, respectively, the 12 mg/day recommended dose. Postnatal development was delayed in rats at a dose of 8 times the 12 mg/day recommended dose [see Data].

Data

Animal Data

Radioactivity was found to cross the placenta following oral administration of labeled doxazosin to pregnant rats. Studies in pregnant rabbits and rats at daily oral doses of up to 41 and 20 mg/kg, respectively (plasma drug concentrations of 10 and 4 times, respectively, the human AUC exposures with a 12 mg/day therapeutic dose), during organogenesis have revealed no evidence of adverse developmental effects. A dosage regimen of 82 mg/kg/day in the rabbit was associated with reduced fetal survival. In peri- and postnatal studies in rats, postnatal development at maternal doses of 40 or 50 mg/kg/day of doxazosin (about 8 times human AUC exposure with a 12 mg/day therapeutic dose) was delayed, as evidenced by slower body weight gain and slightly later appearance of anatomical features and reflexes.

8.2 Lactation

Risk Summary

CARDURA XL is not indicated for use in females and is not indicated for the treatment of hypertension. Doxazosin is present in human milk. There is no information on the effects of CARDURA XL on the breastfeed infant or the effects on milk production.

8.4 Pediatric Use

The safety and effectiveness of CARDURA XL in pediatric patients have not been established.

8.5 Geriatric Use

The incidence of hypotension with CARDURA XL use appears to be age related and more prevalent in patients 70 years or older. At steady state, increases of 27% in maximum plasma concentrations (Cmax) and 34% in the area under the concentration-time curve (AUC) were seen in the elderly (> 65 years old) compared to the young [see Clinical Pharmacology (12.3)].

Of the 666 patients with BPH who received CARDURA XL in the two controlled clinical efficacy and safety studies, 325 patients (49%) were 65 years of age or older. One hundred thirty-six patients treated with CARDURA XL (20%) were > 70 years of age.

In these two studies, the cumulative incidence of hypotension appeared to be age related. The reason for an increased incidence of hypotension in patients older than 70 years of age may be related to a modest increase in systemic exposure to doxazosin [see Clinical Pharmacology (12.3)], to an increased propensity to orthostasis in the elderly, or to an enhanced sensitivity to vasodilatory agents in the elderly. The incidence of hypotension reported as an adverse reaction was higher in patients 70 years of age and older (4/136; 2.9%) as compared to patients < 70 years of age (7/530; 1.3%).

8.6 Hepatic Impairment

Since there is no clinical experience in patients with severe hepatic impairment, use in these patients is not recommended. CARDURA XL should be administered with caution to patients with mild or moderate hepatic impairment [see Warnings and Precautions (5.6), Clinical Pharmacology (12.3)].

10 OVERDOSAGE

There is no experience with CARDURA XL overdosage. Overdosage experience with the doxazosin IR is limited. Two adolescents who each intentionally ingested 40 mg doxazosin IR with diclofenac or paracetamol were treated with gastric lavage with activated charcoal and made full recoveries. A two-year-old child who accidentally ingested 4 mg doxazosin IR was treated with gastric lavage and remained normotensive during the five-hour emergency room observation period. A six-month-old child accidentally received a crushed 1 mg tablet of doxazosin IR and was reported to have been drowsy. A 32-year-old female with chronic renal failure, epilepsy, and depression intentionally ingested 60 mg doxazosin IR (blood level 0.9 µg/mL; normal values in hypertensives = 0.02 µg/mL); death was attributed to a grand mal seizure resulting from hypotension. A 39-year-old female who ingested 70 mg doxazosin IR, alcohol, and Dalmane® (flurazepam) developed hypotension which responded to fluid therapy.

The most likely manifestation of overdosage would be hypotension, for which the usual treatment would be intravenous infusion of fluid, keeping the patient in the supine position, and in certain circumstances, the administration of vasopressors. As doxazosin is highly protein bound, dialysis would not be indicated.

11 DESCRIPTION

CARDURA XL contains doxazosin which is a quinazoline compound with the chemical name 1-(4-amino-6,7-dimethoxy-2-quinazolinyl)-4-(1,4-benzodioxan-2-ylcarbonyl) piperazine methanesulfonate. The empirical formula for doxazosin mesylate is C23H25N5O5 • CH4O3S and the molecular weight is 547.6. It has the following structure:

CARDURA XL is an extended-release tablet for oral use and is designed to deliver 4 or 8 mg of doxazosin as the free base. Each 4 and 8 mg tablet contains 5.1 and 10.2 mg doxazosin mesylate (includes a 5% overage) to ensure the labeled dose of 4 and 8 mg doxazosin as the free base (equivalent to 4.9 and 9.8 mg of doxazosin mesylate), is delivered. The inactive ingredients for CARDURA XL are black iron oxide, cellulose acetate, hypromellose, Macrogol®, magnesium stearate, pharmaceutical glaze, polyethylene oxide, red ferric oxide, sodium chloride and titanium dioxide.

CARDURA XL System Components and Performance

CARDURA XL is similar in appearance to a conventional tablet. It consists, however, of an osmotically active drug core surrounded by a semipermeable membrane. The core itself is divided into two layers: an “active” layer containing the drug, and a “push” layer containing pharmacologically inert (but osmotically active) components. The membrane surrounding the tablet is permeable to water, but not to drug or osmotic excipients. As water from the gastrointestinal tract enters the tablet, pressure increases in the osmotic layer and “pushes” against the drug layer, resulting in the release of drug through a small, laser-drilled orifice in the membrane on the drug side of the tablet.

CARDURA XL utilizes GITS (Gastrointestinal Therapeutic System) which is designed to provide a controlled rate of delivery of doxazosin into the gastrointestinal lumen which is independent of pH or gastrointestinal (GI) motility. The function of CARDURA XL depends upon the existence of an osmotic gradient between the contents of the bi-layer core and fluid in the GI tract. Drug delivery is essentially constant as long as the osmotic gradient remains constant, and then gradually falls to zero. The biologically inert components of the tablet remain intact during GI transit and are eliminated in the feces as an insoluble shell.

12 CLINICAL PHARMACOLOGY

12.1 Mechanism of Action

The symptoms associated with benign prostatic hyperplasia (BPH), such as urinary frequency, nocturia, weak stream, hesitancy, and incomplete emptying are related to two components, anatomical (static) and functional (dynamic). The static component is related to an increase in prostate size caused, in part, by a proliferation of smooth muscle cells in the prostatic stroma. However, the severity of BPH symptoms and the degree of urethral obstruction do not correlate well with the size of the prostate. The dynamic component of BPH is associated with an increase in smooth muscle tone in the prostate and bladder neck. The degree of tone in this area is mediated by the alpha1 adrenoceptor, which is present in high density in the prostatic stroma, prostatic capsule, and bladder neck. Blockade of the alpha1 receptor decreases urethral resistance and may relieve the BPH symptoms and improve urine flow. Doxazosin mesylate is a selective inhibitor of the alpha1-subtype of alpha adrenergic receptors. In the human prostate, doxazosin mesylate antagonizes phenylephrine (alpha1 agonist)-induced contractions, in vitro, and binds with high affinity to the alpha1A adrenoceptor.

12.2 Pharmacodynamics

Administration of CARDURA XL to patients with symptomatic BPH resulted in a statistically significant improvement in maximum urinary flow rate [see Clinical Studies (14.1)].

12.3 Pharmacokinetics

The pharmacokinetics of CARDURA XL is different from that of doxazosin IR. CARDURA XL provides a controlled release of doxazosin over a 24-hour period.

Absorption

Pharmacokinetic parameters describing absorption following 4 and 8 mg CARDURA XL daily doses are reported in Table 2 below. The relative bioavailability of CARDURA XL compared with doxazosin IR was 54% at the 4 mg dose and 59% for the 8 mg dose.

TABLE 2
Mean (±SD) Plasma Concentration of Doxazosin at Steady State in Healthy Volunteers: Pharmacokinetic Parameters
Parameter | CARDURA XL; (4 mg) | CARDURA XL; (8 mg)
Cmax (ng/mL) | 10.1 ± 5.6 | 25.8 ± 12.1
AUC(0 - ∞) | 183 ± 85.5 | 472 ± 170.8
Tmax (h) | 8 ± 3.7 | 9 ± 4.7

Food Effect

As illustrated in Figure 1, the plasma Cmax and AUC were approximately 32% and 18% higher, respectively, after CARDURA XL was administered in the fed state compared with the fasted state. In order to provide the most consistent exposure, CARDURA XL should be administered with breakfast [see Dosage and Administration (2.1)].

Figure 1: Mean (+SD) Plasma Concentration of Doxazosin Following Single Oral Doses of 8 mg CARDURA XL (Fed and Fasted)

GI Retention Time Effect

Markedly reduced GI retention times (e.g., short bowel syndrome) may influence the pharmacokinetics of CARDURA XL and possibly result in lower plasma concentrations. Conversely, markedly prolonged GI retention times (e.g., chronic constipation) can increase systemic exposure to doxazosin and potentially result in increased adverse reactions [see Warnings and Precautions (5.3)].

Distribution

At the plasma concentrations achieved by therapeutic doses, approximately 98% of the circulating drug is bound to plasma proteins.

Metabolism

Doxazosin is extensively metabolized in the liver. In vitro studies suggest that the primary pathway for elimination is via CYP 3A4; however, CYP 2D6 and CYP 2C9 metabolic pathways also exist to a lesser extent. No in vivo drug interaction studies have been performed with CARDURA XL. Although several active metabolites of doxazosin have been identified, the pharmacokinetics of these metabolites has not been characterized [see Drug Interactions (7)].

Excretion

In a study of two subjects administered radiolabeled doxazosin IR 2 mg orally and 1 mg intravenously on two separate occasions, approximately 63% of the dose was eliminated in the feces and 9% of the dose was found in the urine. On average, only 4.8% of the dose was excreted as unchanged drug in the feces and only a trace of the total radioactivity in the urine was attributed to unchanged drug. The apparent elimination half-life of CARDURA XL is 15-19 hours.

Drug-Drug Interactions

No in vivo drug-drug interaction studies have been performed to assess the effect of concomitant medications on the pharmacokinetics of CARDURA XL or to assess the effect of CARDURA XL on the pharmacokinetics of other drugs. In vitro studies suggest that doxazosin is a substrate of CYP 3A4. Caution should be exercised when concomitantly administering CARDURA XL with a strong CYP 3A4 inhibitor, such as atazanavir, clarithromycin, indinavir, itraconazole, ketoconazole, nefazodone, nelfinavir, ritonavir, saquinavir, telithromycin, or voriconazole.

In one placebo-controlled trial in normal volunteers, the administration of a single 1 mg dose of doxazosin IR on day 1 of a four-day regimen of cimetidine (400 mg twice daily) resulted in a 10% increase in the mean AUC of doxazosin, a 6% increase in mean Cmax of doxazosin, and no significant change in mean half-life of doxazosin. Based upon the differences in dose and formulation, the applicability of these results to CARDURA XL is unknown. Otherwise, the interaction potential with other inhibitors or substrates of CYP enzymes has not been determined. Pharmacodynamic interactions between CARDURA XL and anti-hypertensive medications or other vasodilating agents have also not been determined. Finally, drugs which reduce gastrointestinal motility leading to markedly prolonged GI retention times (e.g., anticholinergic agents) may increase systemic exposure to doxazosin.

Use in Specific Populations

Geriatric

In a study to assess the effect of age on the pharmacokinetics of CARDURA XL, increases of 27% in plasma Cmax and 34% in the plasma AUC were seen at steady state in the elderly (> 65 years old) compared to the young [see Use in Specific Populations (8.5)].

Hepatic Impairment

Administration of a single 2 mg dose of doxazosin IR to patients with mild hepatic impairment (Child-Pugh Class A) showed a 40% increase in exposure to doxazosin compared to patients without hepatic impairment. No studies have been performed to assess the effect of hepatic impairment on the pharmacokinetics of CARDURA XL. Use in patients with severe hepatic impairment is not recommended. CARDURA XL should be administered with caution to patients with evidence of mild or moderately impaired hepatic function or to patients receiving drugs known to influence hepatic metabolism.

13 NONCLINICAL TOXICOLOGY

13.1 Carcinogenesis, Mutagenesis, Impairment of Fertility

Carcinogenesis and Mutagenesis

Doxazosin mesylate was not carcinogenic to rats or mice when administered daily for 2 years at doses up to 40 mg/kg/day or 120 mg/kg/day, respectively. Systemic drug exposures, as measured by AUC, were approximately 34-fold in rats and 16-fold in mice above the exposures at the maximum human recommended dose (MHRD) of 8 mg CARDURA XL.

Doxazosin base was not mutagenic in the in vitro bacterial Ames assays, the chromosomal aberration assay in human lymphocytes, or the mouse lymphoma assay. Doxazosin was not clastogenic in the in vivo mouse micronucleus assay. Doxazosin mesylate has not been evaluated for genotoxicity.

Fertility in Males

Studies in rats after oral administration of doxazosin base showed reduced fertility in males, which was reversible after two weeks of treatment termination at doxazosin base exposure of 13-fold above the human exposure (AUC) at the MHRD of 8 mg CARDURA XL. There have been no reports of any effects of doxazosin on male fertility in humans.

13.2 Animal Toxicology and Pharmacology

Studies in Sprague-Dawley rats after 6, 12, and 18 months, and in CD-1 mice after 18 months of dietary administration, showed an increased incidence of myocardial necrosis or fibrosis at doxazosin base exposure of 26-fold above the human exposure (AUC) at the MHRD of 8 mg CARDURA XL. No cardiotoxicity was observed in dogs or Wistar rats after 12 months of oral dosing at doxazosin base exposures of 65- and 85-fold, respectively, above the human exposure (Cmax) at the MHRD of 8 mg CARDURA XL. There is no evidence that similar lesions occur in humans.

14 CLINICAL STUDIES

14.1 Studies in Patients with BPH

Two controlled clinical studies were conducted with CARDURA XL in BPH patients, followed by an open-label extension study. Study 1 was a randomized, double-blind, parallel-group, placebo- and active-controlled study that compared the safety and efficacy of CARDURA XL (4 or 8 mg/day) with that of doxazosin IR (1, 2, 4, or 8 mg/day) and placebo over 13 weeks in 795 BPH patients, of whom 317 were randomized to CARDURA XL. Study 2 was a randomized, double-blind, parallel-group, active-controlled study that compared the safety and efficacy of CARDURA XL (4 or 8 mg/day) with that of doxazosin IR (1, 2, 4, or 8 mg/day) over 13 weeks in 680 BPH patients, of whom 350 were randomized to CARDURA XL.

In both studies, men aged 50-80 years with symptomatic benign prostatic hyperplasia (BPH) were enrolled. Symptomatic BPH was defined as a total score of at least 12 points on the 35-point International Prostate Symptom Score (IPSS) and a maximum urinary flow rate of ≤ 15 mL/sec but no less than 5 mL/sec (total voided volume ≥ 150 mL). In these two studies, conducted in a total of 1475 patients, the mean age was 64 years (range 47-83 years). Patients were Caucasian (96%), Black (1.5%), Asian (1.5%), and of Other ethnicity (1%).

In both studies, CARDURA XL dosing was initiated after a 2-week placebo run-in period at 4 mg per day increasing to 8 mg per day after 7 weeks of treatment if adequate response (defined as having both an increase in maximum urinary flow rate of at least 3 mL/sec and a decrease in total IPSS of at least 30% from baseline) was not seen. Doxazosin IR was titrated from an initial dose of 1 mg daily to 2 mg daily after 1 week with the option to increase to 4 mg daily after 3 weeks and then to a maximum of 8 mg daily after 7 weeks if an adequate response was not seen. The final daily dose of CARDURA XL was 4 mg in 43% of patients and 8 mg in 57% of patients. The final daily dose of doxazosin IR was 1 mg in 1%, 2 mg in 12%, 4 mg in 30%, and 8 mg in 57% of patients.

There were two primary efficacy variables in each of these two controlled clinical studies: the total International Prostate Symptom Score (IPSS) and the peak urinary flow rate (Qmax). The IPSS consists of seven questions that assess the severity of both irritative (frequency, urgency, nocturia) and obstructive (incomplete emptying, stopping and starting, weak stream, and pushing or straining) symptoms, with possible total scores ranging from 0 to 35. The Qmax was measured in both studies just prior to the next dose. The results for total symptom score are given in Table 3, and for maximum urinary flow rate in Table 4.

TABLE 3
TOTAL INTERNATIONAL PROSTATE SYMPTOM SCORE (IPSS) [Derived from IPSS questionnaire (range 0-35)]
 | N | MEAN BASELINE; (± SD) | MEAN CHANGE; (± SE) [Mean change from baseline to Week 13]
STUDY 1
Placebo | 151 | 17.9 ± 4.3 | -6.1 ± 0.41
CARDURA XL | 310 | 17.7 ± 4.3 | -8.0 ± 0.30 [Statistically significant difference (p < 0.001) vs. placebo]
Doxazosin IR | 311 | 17.8 ± 4.5 | -8.4 ± 0.29
STUDY 2
CARDURA XL | 330 | 18.4 ± 5.0 | -8.1 ± 0.30
Doxazosin IR | 313 | 18.4 ± 4.8 | -7.9 ± 0.31

TABLE 4
MAXIMUM FLOW RATE (mL/sec)
 | N | MEAN BASELINE; (± SD) | MEAN CHANGE; (± SE) [Mean change from baseline to Week 13]
STUDY 1
Placebo | 151 | 9.8 ± 2.6 | 0.8 ± 0.32
CARDURA XL | 300 | 10.3 ± 2.6 | 2.6 ± 0.24 [Statistically significant difference (p < 0.001) vs. placebo]
Doxazosin IR | 303 | 10.1 ± 2.7 | 2.2 ± 0.23
STUDY 2
CARDURA XL | 322 | 10.5 ± 2.6 | 2.7 ± 0.27
Doxazosin IR | 314 | 10.6 ± 2.6 | 2.7 ± 0.27

Mean changes in IPSS scores for CARDURA XL and placebo in Study 1 are summarized in Figure 2.

FIGURE 2: Mean Total IPSS (± SE) by Week in Study 1

Mean changes in maximum urinary flow rate (Qmax) for both CARDURA XL and placebo in Study 1 are summarized in Figure 3.

FIGURE 3: Mean Maximum Urinary Flow Rate (mL/sec) (± SE) by Week in Study 1

16 HOW SUPPLIED/STORAGE AND HANDLING

CARDURA XL (doxazosin) extended-release tablets is available as 4 mg (white, imprinted with CXL 4) and 8 mg (white, imprinted with CXL 8) tablets.

Bottle of 30: 4 mg (NDC 58151-078-93)
Bottle of 30: 8 mg (NDC 58151-079-93)

Storage

Recommended Storage: Store at 25°C (77°F); excursions permitted to 15-30°C (59-86°F) [see USP Controlled Room Temperature].

17 PATIENT COUNSELING INFORMATION

See FDA-approved patient labeling (Patient Information)

17.1 Postural Hypotension

Patients should be told about the possible occurrence of symptoms related to postural hypotension, such as dizziness or syncope, when beginning therapy or when increasing dosage strength of CARDURA XL. Patients should be cautioned about driving, operating machinery, or performing hazardous tasks during this period, until the drug’s effect has been determined.

17.2 Priapism

Inform the patient about the possibility of priapism as a result of treatment with CARDURA XL extended-release tablets and other similar medications. Patients should be informed that this reaction is extremely rare, but if not brought to immediate medical attention, can lead to permanent erectile dysfunction.

17.3 Tablet Administration

Patients should be informed that CARDURA XL extended-release tablets should be swallowed whole. Patients should not chew, divide, cut, or crush tablets.

17.4 Dosing Interval

CARDURA XL should be taken each day with breakfast.

17.5 Tablet Elimination

Patients should not be concerned if they occasionally notice in their stool something that looks like a tablet. In the CARDURA XL extended-release tablet, the medication is contained within a nonabsorbable shell designed to release the drug at a controlled rate. When this process is completed, the empty tablet is eliminated from the body.

Distributed by:
Viatris Specialty LLC
Morgantown, WV 26505 U.S.A.

© 2023 Viatris Inc.

CARDURA is a registered trademark of Viatris Specialty LLC, a Viatris Company

The brands listed are trademarks of their respective owners.

UPJ:CRDAXL:R1

PATIENT INFORMATION

CARDURA® XL (kar-DUR-a eks el)
(doxazosin)
Tablets

Read this Patient Information leaflet before you start taking CARDURA XL and each time you get a refill. There may be new information. This information does not take the place of talking to your healthcare provider about your medical condition or your treatment.

What is CARDURA XL?

CARDURA XL is a prescription medicine called an “alpha-blocker”. CARDURA XL is used to treat the symptoms of benign prostatic hyperplasia (BPH). CARDURA XL may help to relax the muscles in the prostate and the bladder which may lessen the symptoms of BPH and improve urine flow.

Before prescribing CARDURA XL, your healthcare provider may examine your prostate gland and do a blood test called a prostate specific antigen (PSA) test to check for prostate cancer. Prostate cancer and BPH can cause the same symptoms. Prostate cancer needs a different treatment.

Some medicines called “alpha-blockers” are used to treat high blood pressure. CARDURA XL is not for the treatment of high blood pressure.

It is not known if CARDURA XL is safe and effective in children.

Who should not take CARDURA XL?

Do not take CARDURA XL if you are allergic to doxazosin, other medications called quinazolines, or any of the ingredients in CARDURA XL. See the end of this leaflet for a complete list of ingredients in CARDURA XL.

What should I tell my healthcare provider before taking CARDURA XL?

Before you take CARDURA XL, tell your healthcare provider if you:

- have or have had low blood pressure, especially after taking another medicine. Signs of low blood pressure are fainting, dizziness, and lightheadedness.
- plan to have cataract surgery
- have stomach problems
- have prostate cancer
- have liver problems
- have heart problems

Tell your healthcare provider about all the medicines you take, including prescription and non-prescription medicines, vitamins, and herbal supplements.

CARDURA XL may affect the way other medicines work, and other medicines may affect how CARDURA XL works.

Especially tell your healthcare provider if you take:

- a medicine to treat an infection
- a medicine to treat HIV
- a medicine to treat depression
- a medicine to treat erectile dysfunction (ED)

Ask your healthcare provider or pharmacist if you are not sure if your medicine is one of those listed above.

Know the medicines you take. Keep a list of them to show your healthcare provider and pharmacist when you get a new medicine.

How should I take CARDURA XL?

- Take CARDURA XL exactly as your healthcare provider tells you to take it.
- Take CARDURA XL 1 time each day with your breakfast.
- Take CARDURA XL tablets whole. Do not chew, divide, cut, or crush CARDURA XL tablets before swallowing. If you cannot swallow CARDURA XL tablets whole, tell your healthcare provider. You may need a different medicine.
- CARDURA XL tablets have an outside shell that helps to release the medicine inside over time. You may see the empty CARDURA XL tablet in your stool (bowel movement). This is normal.
- If you take too much CARDURA XL, call your healthcare provider or go to the nearest hospital emergency room right away.

What should I avoid while taking CARDURA XL?

Do not drive, operate machinery, or do other dangerous activities until you know how CARDURA XL affects you. CARDURA XL can cause dizziness, weakness, or fainting.

What are the possible side effects of CARDURA XL?

CARDURA XL may cause serious side effects including:

- a sudden drop in blood pressure (postural hypotension). Postural hypotension can happen at any time while you take CARDURA XL. The chance of having postural hypotension is higher a few hours after you take CARDURA XL or if you start taking a higher dose.
  Symptoms of postural hypotension may happen after you stand up from a lying or sitting position and may include:
  - dizziness or
  - fainting or
  - feeling light-headed
You should get up slowly from a chair or bed until you know how CARDURA XL will affect you. If you begin to feel dizzy or lightheaded, sit or lie down with your legs and feet up. If your symptoms do not get better call your healthcare provider.
- intraoperative floppy iris syndrome (IFIS). IFIS can happen during eye surgery to people who are taking or have taken alpha-blockers such as CARDURA XL. If you have an eye surgery for a clouding of the eye (cataract) planned, tell your eye doctor that you are using CARDURA XL or have taken an alpha-blocker before.
- blockage of the digestive tract. There have been rare reports of symptoms of blockage in the digestive tract in patients with prior history of narrowing or blockage of the digestive tract. These symptoms are severe and persistent abdominal pain/cramping/bloating. If you know you have a narrowing of your digestive tract and you experience these symptoms, contact your healthcare provider.
- prolonged erection of the penis. Extremely rarely, CARDURA XL and similar medications have caused painful erection of the penis, sustained for hours and unrelieved by sexual intercourse or masturbation. This condition is serious, and if untreated it can be followed by permanent inability to have an erection. If you have a prolonged abnormal erection, call your doctor or go to an emergency room as soon as possible.

The most common side effects of CARDURA XL include:

- tiredness
- headache
- low blood pressure
- dizziness

Call your healthcare provider if you get any side effect that bothers you or that does not go away.

These are not all the possible side effects of CARDURA XL. For more information ask your healthcare provider or pharmacist.

Call your doctor for medical advice about side effects. You may report side effects to FDA at 1-800-FDA-1088.

How should I store CARDURA XL?

- Store CARDURA XL at 59°F to 86°F (15°C to 30°C).

Keep CARDURA XL and all medicines out of reach of children.

General information about the safe and effective use of CARDURA XL.

Medicines are sometimes prescribed for purposes other than those listed in a Patient Information leaflet. Do not use CARDURA XL for a condition for which it was not prescribed. Do not give CARDURA XL to other people, even if they have the same symptoms you have. It may harm them.

This Patient Information leaflet summarizes the most important information about CARDURA XL. If you would like more information, talk with your healthcare provider. You can ask your healthcare provider or pharmacist for information about CARDURA XL that is written for health professionals.

For more information, call Viatris at 1-877-446-3679 (1-877-4-INFO-RX).

What are the ingredients in CARDURA XL?

Active Ingredient: doxazosin

Inactive Ingredients: black iron oxide, cellulose acetate, hypromellose, Macrogol®, magnesium stearate, pharmaceutical glaze, polyethylene oxide, red ferric oxide, sodium chloride and titanium dioxide.

Distributed by:
Viatris Specialty LLC
Morgantown, WV 26505 U.S.A.

© 2023 Viatris Inc.

CARDURA is a registered trademark of Viatris Specialty LLC, a Viatris Company

The brands listed are trademarks of their respective owners.

UPJ:PL:CRDAXL:R1
Revised: 5/2023

PRINCIPAL DISPLAY PANEL – 4 mg

NDC 58151-078-93

Cardura® XL
(doxazosin)
extended-release tablets
4 mg*

30 Tablets Rx only

Store at 25ºC (77ºF);
excursions permitted to
15-30ºC (59-86ºF)
[see USP Controlled Room
Temperature].

PROTECT FROM MOISTURE
AND HUMIDITY.

DOSAGE AND USE
See accompanying
prescribing information.

*Each tablet contains 5.1 mg
doxazosin mesylate which
includes an overage to provide
4 mg doxazosin as a free base.

Distributed by:
Viatris Specialty LLC
Morgantown, WV 26505 U.S.A.

© 2023 Viatris Inc.

RUPJ078H

PRINCIPAL DISPLAY PANEL – 8 mg

NDC 58151-079-93

Cardura® XL
(doxazosin)
extended-release tablets
8 mg*

30 Tablets Rx only

Store at 25ºC (77ºF);
excursions permitted to
15-30ºC (59-86ºF)
[see USP Controlled Room
Temperature].

PROTECT FROM MOISTURE
AND HUMIDITY.

DOSAGE AND USE
See accompanying
prescribing information.

*Each tablet contains 10.2 mg
doxazosin mesylate which
includes an overage to provide
8 mg doxazosin as a free base.

Distributed by:
Viatris Specialty LLC
Morgantown, WV 26505 U.S.A.

© 2023 Viatris Inc.

RUPJ079H